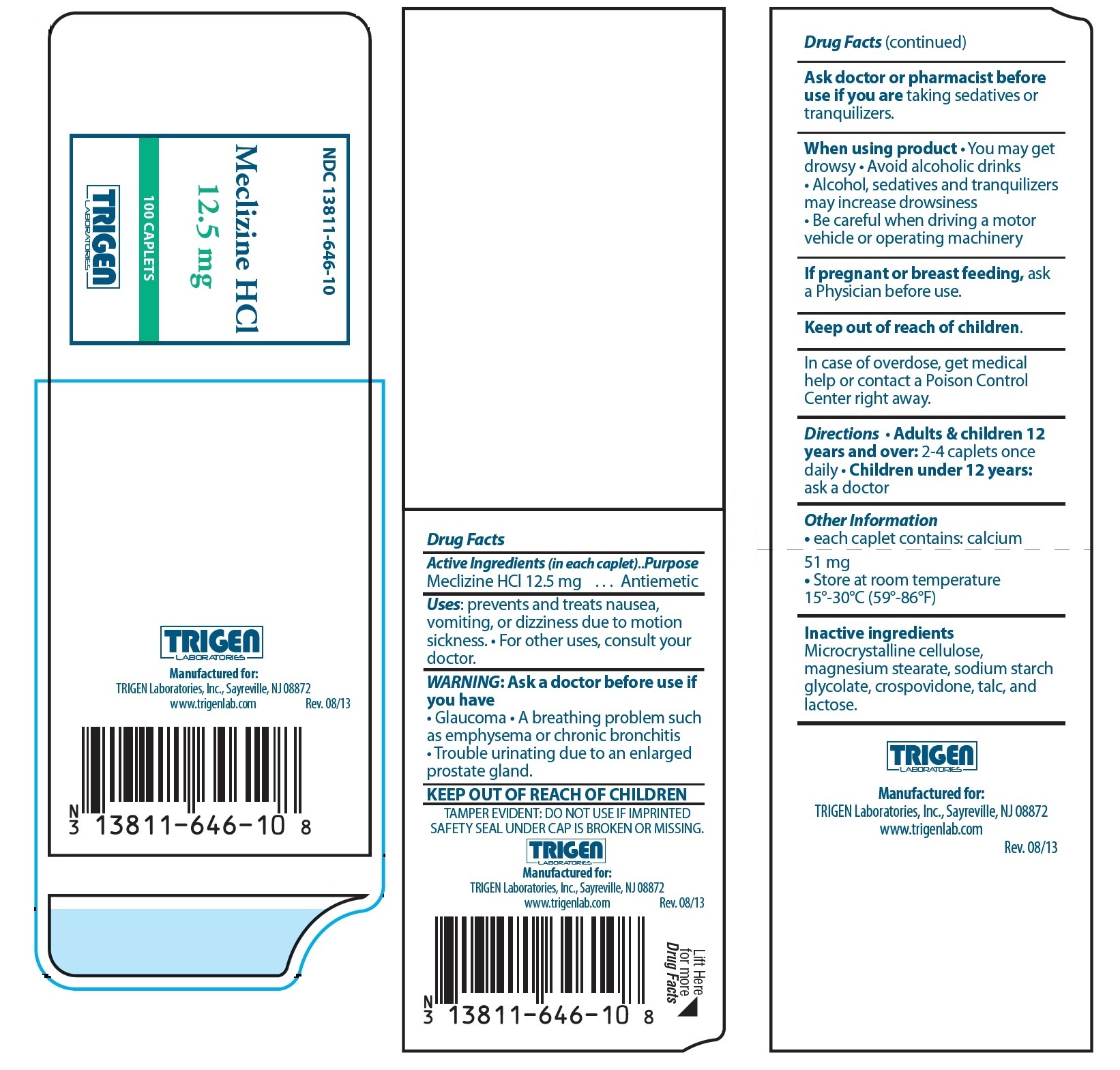 DRUG LABEL: Meclizine HCl
NDC: 13811-646 | Form: TABLET
Manufacturer: Trigen Laboratories, Inc.
Category: otc | Type: HUMAN OTC DRUG LABEL
Date: 20130915

ACTIVE INGREDIENTS: MECLIZINE HYDROCHLORIDE 12.5  mg/1 1
INACTIVE INGREDIENTS: CELLULOSE, MICROCRYSTALLINE; MAGNESIUM STEARATE; SODIUM STARCH GLYCOLATE TYPE A CORN; POVIDONE K30; TALC; LACTOSE

DRUG FACTS

Active Ingredients (in each caplet)

Meclizine HCl 12.5 mg

Purpose

Antiemetic

Uses:

prevents and treats nausea, vomiting, or dizziness due to motion sickness.• For other uses, consult your doctor.

WARNING: Ask a doctor before use if you have

• Glaucoma • A breathing problem such as emphysema or chronic bronchitis • Trouble urinating due to an enlarged prostate gland.

Ask doctor or pharmacist before use if you are taking sedatives or tranquilizers.

When using product

• You may get drowsy • Avoid alcoholic drinks • Alcohol, sedatives and tranquilizers may increase drowsiness • Be careful when driving a motor vehicle or operating machinery

PREGNANCY OR BREAST FEEDING

If pregnant or breast feeding, ask a Physician before use.

Keep out of reach of children.

In case of overdose, get medical help or contact a Poison Control Center right away.

Directions

• Adults & children 12 years and over: 2-4 caplets once daily

• Children under 12 years: ask a doctor

Other Information

• each caplet contains: calcium 51 mg

• Store at room temperature 15°-30°C (59°-86°F)

Inactive ingredients

Microcrystalline cellulose, magnesium stearate, sodium starch glycolate, crospovidone, talc, and lactose.

TAMPER EVIDENT: DO NOT USE IF IMPRINTED SAFETY SEAL UNDER CAP IS BROKEN OR MISSING.

TRIGEN
LABORATORIES

Manufactured for:
TRIGEN Laboratories, Inc., Sayreville, NJ 08872
www.trigenlab.com
Rev. 08/13

PRINCIPAL DISPLAY PANEL - 12.5 mg Caplet Label

NDC 13811-646-10

Meclizine HCl
12.5 mg

100 CAPLETS

TRIGEN
LABORATORIES

Manufactured for:
TRIGEN Laboratories, Inc., Sayreville, NJ 08872
www.trigenlab.com
Rev. 08/13